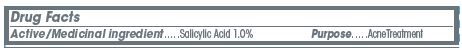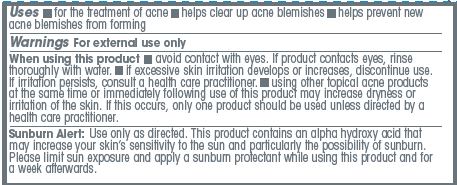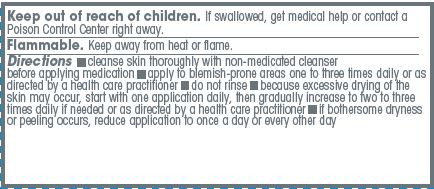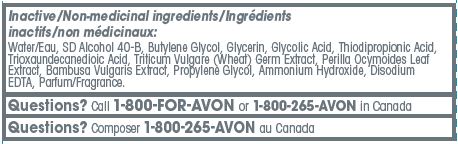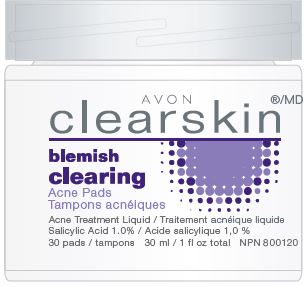 DRUG LABEL: Clearskin
NDC: 10096-0186 | Form: LIQUID
Manufacturer: New Avon LLC
Category: otc | Type: HUMAN OTC DRUG LABEL
Date: 20190101

ACTIVE INGREDIENTS: SALICYLIC ACID 10 mg/1 g
INACTIVE INGREDIENTS: WATER

Clearskin Blemish Clearing Acne Pads

Uses

- for the treatment of acne
- helps clear up acne blemishes
- helps prevent new acne blemishes from forming

Warnings
For external use only

When using this product

- avoid contact with eyes. If product contacts eyes, rinse thoroughly with water.
- if excessive skin irritation develops or increases, discontinue use. If irritation persists, consult a health care practitioner.
- when using other topical acne products at the same time or immediately following use of this product may increase dryness or irritation of the skin. If this occurs, only one product should be used unless directed by a health care practitioner.

USER SAFETY WARNINGS

Sunburn Alert: Use only as directed. This product contains an alpha hydroxy acid that may increase your skin's sensitivity to the sun and particularly the possibility of sunburn. Please limit sun exposure and apply a sunburn protectant while using this product and for a week afterwards.

Keep out of reach of children. If swallowed, get medical help or
contact a Poison Control Center right away.

STORAGE AND HANDLING

Flammable. Keep away from heat or flame.

Directions

- cleanse skin thoroughly with non-medicated cleanser before applying medication
- apply to blemish-prone areas one to three times daily or as directed by a health care practitioner
- do not rinse
- because excessive drying of the skin may occur, start with one application daily, then gradually increase to two to three time daily if needed or as directed by a health care practitioner
- if bothersome dryness or peeling occurs, reduce application to once a day or every other day

Inactive/Non-medicinal ingredients/Ingrédients inactifs/non médicinaux
Water/Eau, SD Alcohol 40-B, Butylene Glycol, Glycerin, Glycolic Acid, Thiodipropionic Acid, Trioxaundecanedioic Acid, Triticum Vulgare (Wheat) Germ Extract, Perilla Ocymoides Leaf Extract, Bambusa Vulgaris Extract, Propylene Glycol, Ammonium Hydroxide, Disodium EDTA, Parfum/Fragrance

QUESTIONS

Questions? Call 1-800-FOR-AVON or 1-800-265-AVON in Canada

ACTIVE INGREDIENT

Active/Medicinal Ingredient.....Salicylic Acid 1.0% Purpose...... Acne Treatment

Purpose... Acne Treatment